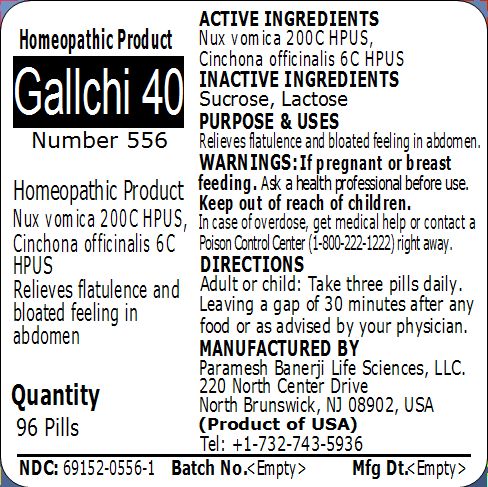 DRUG LABEL: Gallchi 40 (Number 556)
NDC: 69152-0556 | Form: PELLET
Manufacturer: Paramesh Banerji Life Sciences LLC
Category: homeopathic | Type: HUMAN OTC DRUG LABEL
Date: 20150307

ACTIVE INGREDIENTS: CINCHONA OFFICINALIS BARK 6 [hp_C]/1 1; STRYCHNOS NUX-VOMICA SEED 200 [hp_C]/1 1
INACTIVE INGREDIENTS: SUCROSE; LACTOSE

Active Ingredients

Nux vomica 200C HPUS, Cinchona officinalis 6C HPUS

Inactive Ingredients

Sucrose, Lactose

Purpose

Relieves flatulence and bloated feeling in abdomen

Uses

Relieves flatulence and bloated feeling in abdomen

Warnings

If pregnant or breast feeding ask a health professional before use.

Keep out of reach of children. In case of overdose, get medical help or contact a Poison Control Center (1-800-222-1222) right away.

Direction

Adult or child: Take three pills daily. Leaving a gap of 30 minutes after any food or as advised by your physician.

Manufactured by

Paramesh Banerji Life Sciences, LLC

220 North Center Drive

North Brunswick, NJ 08902, USA

Product of USA

Tel: +1-732-743-5936

Principal Display Panel

Homeopathic Product

Gallchi 40

Number 556

Homeopathic Product

Nux vomica 200C HPUS, Cinchona officinalis 6C HPUS

Relieves flatulence and bloated feeling in abdomen

Quantity

96 Pills